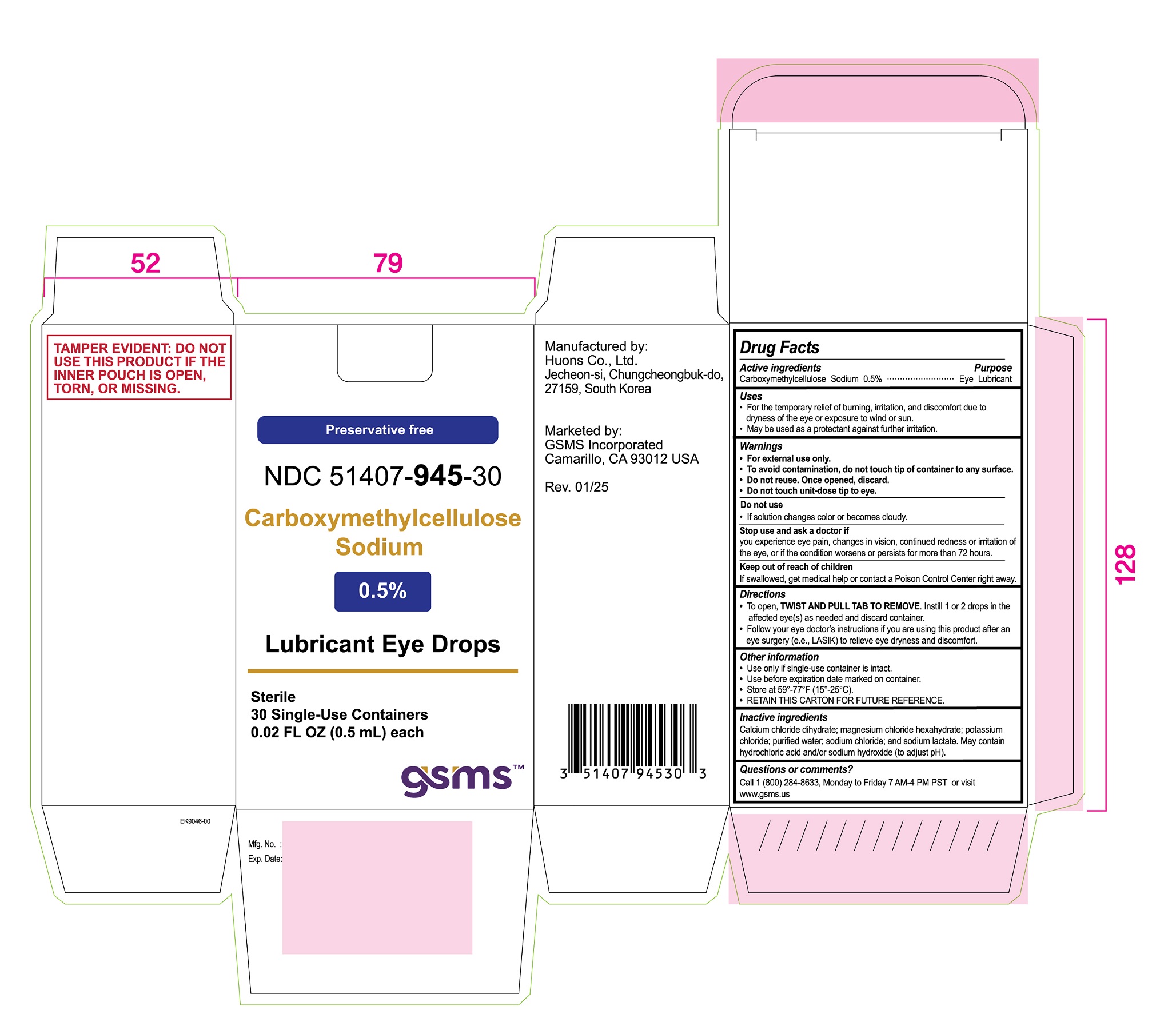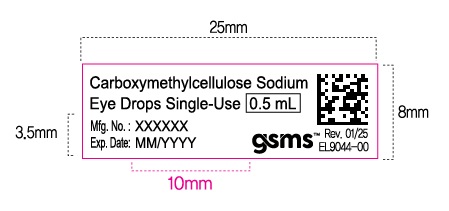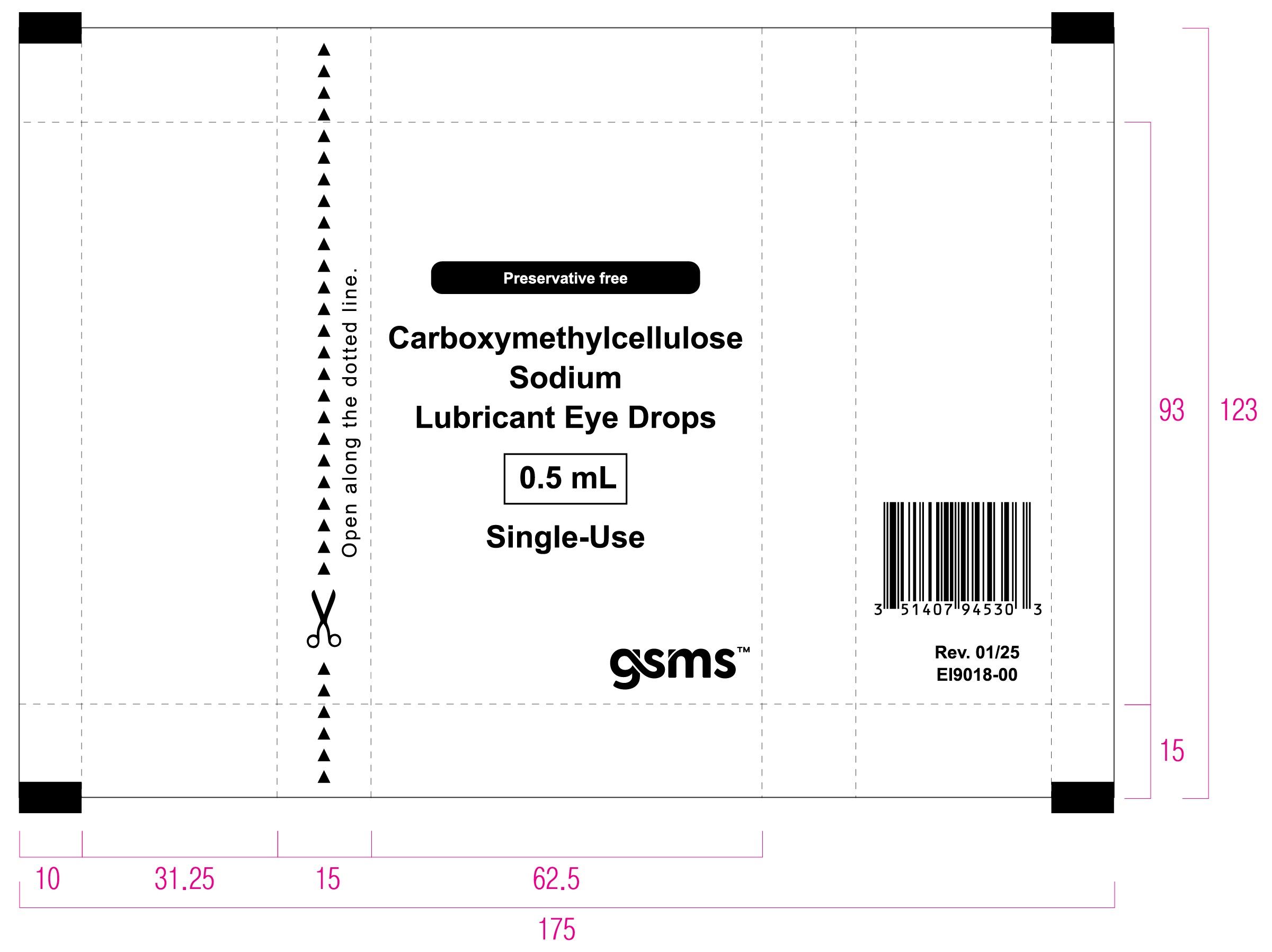 DRUG LABEL: Carboxymethylcellulose Sodium 0.5%
NDC: 51407-945 | Form: SOLUTION/ DROPS
Manufacturer: Golden State Medical Supply, Inc.
Category: otc | Type: HUMAN OTC DRUG LABEL
Date: 20250225

ACTIVE INGREDIENTS: CARBOXYMETHYLCELLULOSE SODIUM 5 mg/1 mL
INACTIVE INGREDIENTS: HYDROCHLORIC ACID; SODIUM CHLORIDE; CALCIUM CHLORIDE; SODIUM LACTATE; SODIUM HYDROXIDE; MAGNESIUM CHLORIDE; POTASSIUM CHLORIDE; WATER

Carboxymethylcellulose Sodium 0.5% Lubricant Eye Drops

Active Ingredients

Carboxymethylcellulose sodium 0.5%

Purpose

Eye lubricant

Uses

- For the temporary relief of burning, irritation, and discomfort due to dryness of the eye or exposure to wind or sun.
- May be used as a protectant against further irritation.

Warnings

- For external use only.
- To avoid contamination, do not touch tip of container to any surface.
- Do not reuse. Once opened, discard.
- Do not touch unit-dose tip to eye.

Do not use

If solution changes color or becomes cloudy.

Stop use and ask a doctor if

you experience eye pain, changes in vision, continued redness or irritation of the eye, or if the condition worsens or persists for more than 72 hours.

Keep out of reach of children

If swallowed, get medical help or contact a Poison Control Center right away.

Directions

- To open, TWIST AND PULL TAB TO REMOVE. Instill 1 or 2 drops in the affected eye(s) as needed and discard container.
- Follow your eye doctor’s instructions if you are using this product after an eye surgery (e.g., LASIK) to relieve eye dryness and discomfort.

Other information

- Use only if single-use container is intact.
- Use before expiration date marked on container.
- Store at 59°-77°F (15°-25°C).
- RETAIN THIS CARTON FOR FUTURE REFERENCE.

Inactive ingredients

Calcium chloride dihydrate; magnesium chloride hexahydrate; potassium chloride; purified water; sodium chloride; and sodium lactate. May contain hydrochloric acid and/or sodium hydroxide (to adjust pH).

Questions or comments?

Call 1 (800) 284-8633, Monday to Friday 7 AM-4PM PST or visit www.gsms.us

TAMPER EVIDENT

DO NOT USE THIS PRODUCT IF THE INNER POUCH IS OPEN, TORN, OR MISSING.

PACKAGE LABEL

Carton

Preservative free

NDC 51407-945-30

Carboxymethylcellulose

Sodium

0.5%

Lubricant Eye Drops

Sterile

30 Single-Use Containers

0.02 FL OZ (0.5 mL) each

gsms

Manufactured by:

Huons Co,, Ltd.

Jecheon-si, Chungcheongbuk-do,

27159. South Korea

Marketed by:

GSMS Incorporated

Camarillo, CA 93012 USA

Rev. 01/25

Pouch

Preservative free

Carboxymethylcellulose

Sodium

Lubricant Eye Drops

0.5 mL

Single-Use

gsms

Open along the dotted line.

Label

Carboxymethylcellulose Sodium

Eye Drops Single-Use 0.5 mL

gsms

Rev. 01/25

EL9044-00